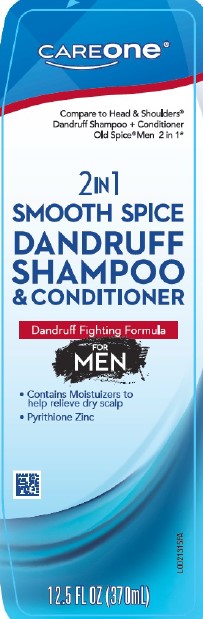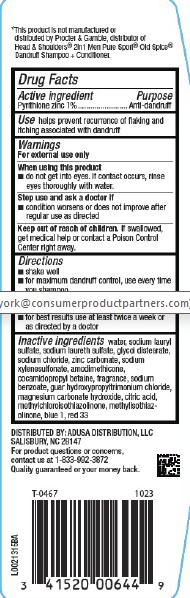 DRUG LABEL: Dandruff
NDC: 72476-253 | Form: SHAMPOO
Manufacturer: Retail Business Services, LLC
Category: otc | Type: HUMAN OTC DRUG LABEL
Date: 20260206

ACTIVE INGREDIENTS: PYRITHIONE ZINC 10 mg/1 mL
INACTIVE INGREDIENTS: SODIUM XYLENESULFONATE; AMODIMETHICONE (800 CST); COCAMIDOPROPYL BETAINE; SODIUM BENZOATE; GUAR HYDROXYPROPYLTRIMONIUM CHLORIDE (1.7 SUBSTITUENTS PER SACCHARIDE); MAGNESIUM CARBONATE HYDROXIDE; CITRIC ACID MONOHYDRATE; METHYLCHLOROISOTHIAZOLINONE; METHYLISOTHIAZOLINONE; FD&C BLUE NO. 1; D&C RED NO. 33; WATER; SODIUM LAURYL SULFATE; SODIUM LAURETH SULFATE; GLYCOL DISTEARATE; SODIUM CHLORIDE; ZINC CARBONATE

Care One 253.001/253AB-AE
Men's Smooth Sea Scent Dandruff Shampoo and Conditioner

Disclaimer

*This product is not manufactured or distributed by Procter & Gamble, distributor of Head & Shoulders®2in1 Men Pure Sport®Old Spice®Dandruff Shampoo + Conditioner.

Active ingredient

Pyrithione zinc 1%

Purpose

Anti-dandruff

Use

helps prevent recurrence of flaking and itching associated with dandruff

Warnings

For external use only

When using this product

- do not get into eyes. If contact occurs, rinse eyes thoroughly with water.

Stop use and ask a doctor if

- condition worsens or does not improve after regular use as directed

Keep out of reach of children.

If swallowed, get medical help or contact a Poison Control Center right away.

Directions

- shake well
- for maximum dandruff control, use every time you shampoo
- wet hair, massage onto scalp, rinse, repeat if desired
- for best results use at least twice a week or as directed by a doctor

Inactive ingredients

water, sodium lauryl sulfate, sodium laureth sulfate, glycol distearate, sodium chloride, zinc carbonate, sodium xylenesulfonate, amodimethicone, cocamidopropyl betaine, fragrance, sodium benzoate, guar hydroxypropyltrimonium chloride, magnesium carbonate hydroxide, citric acid, methylchloroisothiazolinone, methylisothiazolinone, blue 1, red 33

ADVERSE REACTION

DISTRIBUTED BY: ADUSA DISTRIBUTION, LLC

SALISBURY, NC 28147

For product questions or concerns, contact us at 1-833-992-3872

Quality guaranteed or your money back

principal display panel

CAREone®

Compare to Head & Shoulders Dandruff Shampoo + Conditioner Old Spice®Men 2in1*

2 in 1 SMOOTH SPICE DANDRUFF SHAMPOO & CONDITIONER

Dandruff Fighting Formula

For Men

- Contains Moisturizes to help relieve dry scalp
- Pyrithione zinc

12.5 FL OZ (370 mL)